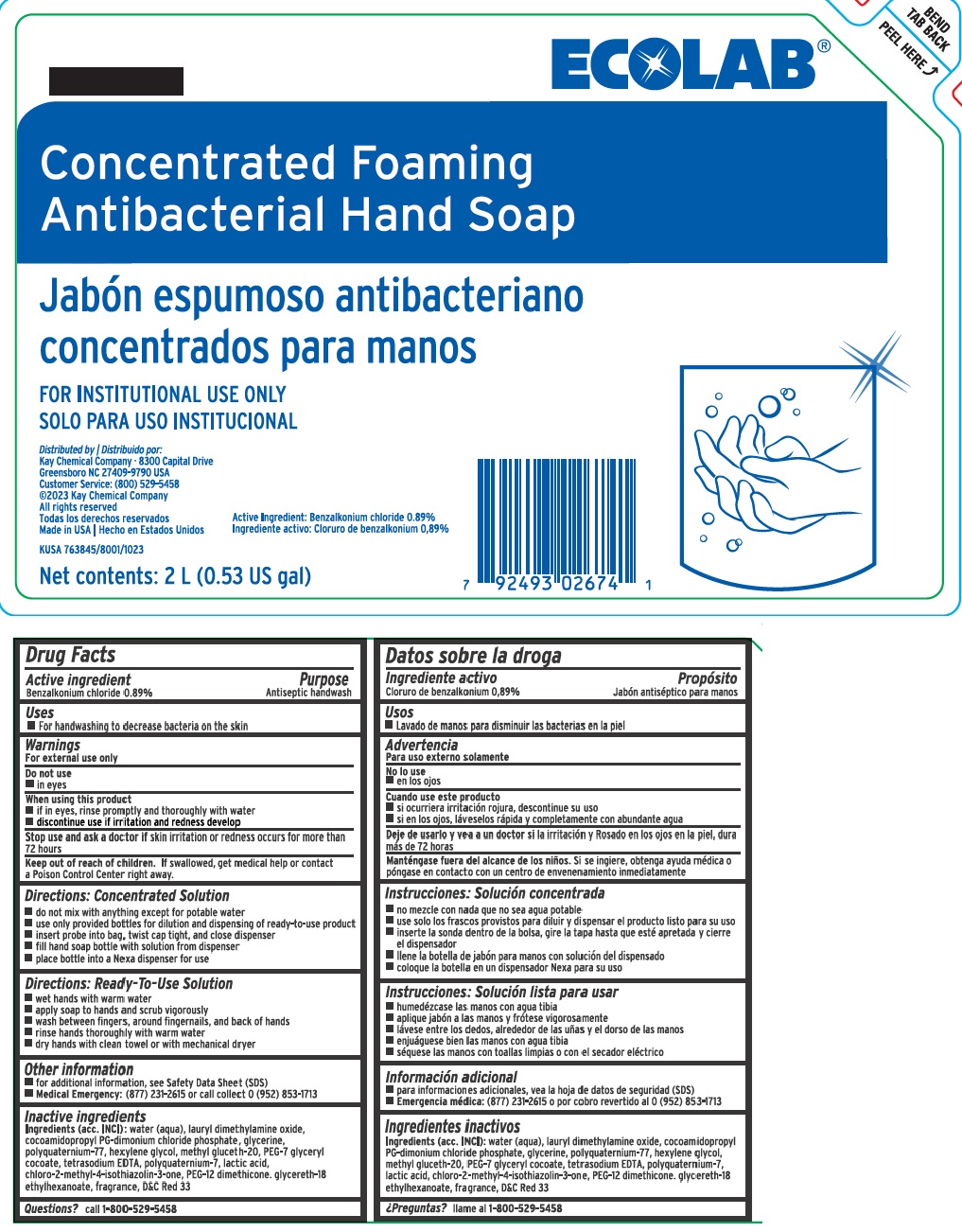 DRUG LABEL: Ecolab Concentrated Foaming Antibacterial Handsoap
NDC: 47593-676 | Form: SOLUTION
Manufacturer: Ecolab Inc.
Category: otc | Type: HUMAN OTC DRUG LABEL
Date: 20251217

ACTIVE INGREDIENTS: BENZALKONIUM CHLORIDE 8.9 mg/1 mL
INACTIVE INGREDIENTS: WATER; LAURAMINE OXIDE; COCAMIDOPROPYL PROPYLENE GLYCOL-DIMONIUM CHLORIDE PHOSPHATE; GLYCERIN; POLYQUATERNIUM-7 (70/30 ACRYLAMIDE/DADMAC; 1600 KD); HEXYLENE GLYCOL; METHYL GLUCETH-20; PEG-7 GLYCERYL COCOATE; EDETATE DISODIUM; LACTIC ACID; METHYLCHLOROISOTHIAZOLINONE; PEG-12 DIMETHICONE; GLYCERETH-18 ETHYLHEXANOATE; D&C RED NO. 33

Drug Facts

Active ingredient

Benzalkonium chloride 1.89%

Purpose

Antiseptic handwash

Uses

- for handwashing to decrease bacteria on the skin

Warnings

For external use only

Do not use

- in eyes

When using this product

- if in eyes, rinse promptly and thoroughly with water
- discontinue use if irritation and redness develop

Stop use and ask a doctor if

- skin irritation or redness occurs for more than 72 hours

Keep out of reach of children. If swallowed, get medical help or contact a Poison Control Center right away.

DOSAGE AND ADMINISTRATION

Directions: Concentrated Solution

- do not mix with anything except for potable water
- use only provided bottles for diution and dispensing of ready-to-use product
- insert probe into bag, twist cap tight, and close dispenser
- fill hand soap bottle with solution from dispenser
- place bottle into a Nexa dispenser for use

Directions: Ready-To-Use Solution

- wet hands with warm water
- apply soap to hands and scrub vigorously
- wash between fingers, around fingernails, and back of hands
- rinse hands thoroughly with warm water
- dry hands with clean towel or with mechanical dryer

Other information

- for additional information, see Safety Data Sheet (SDS)
- Medical Emergency: (877) 231-2615 or call collect 0 (952) 853-1713

INACTIVE INGREDIENT

Ingredients (acc. INCI): water (aqua), lauryl dimethylamine oxide, cocoamidopropyl PG-dimonium chloride phosphate, glycerine, polyquaternium-77, hexylene glycol, methyl gluceth-20, PEG-7 glyceryl cocoate, tetrasodium EDTA, polyquaternium-7, lactic acid, chloro-2-methyl-4-isothiazolin-3-one, PEG-12 dimethicone. glycereth-18 ethylhexanoate, fragrance, D&C Red 33

Questions? call 1-800-529-5458

Principal Display Panel and Representative Label

ECOLAB®

Concentrated Foaming Antibacterial Hand Soap

FOR INSTITUTIONAL USE ONLY

Distributed by | Distribuido por:
Kay Chemical Company · 8300 Capital Drive
Greensboro NC 27409-9790 USA
Customer Service: (800) 529-5458
©2016 Kay Chemical Company
All rights reserved | Todas los derechos reservados
Made in USA | Hecho en Estados Unidos

763845-00 KUSA 7+3845/8000/0116

Net contents: 2L (0.53 US Gal)